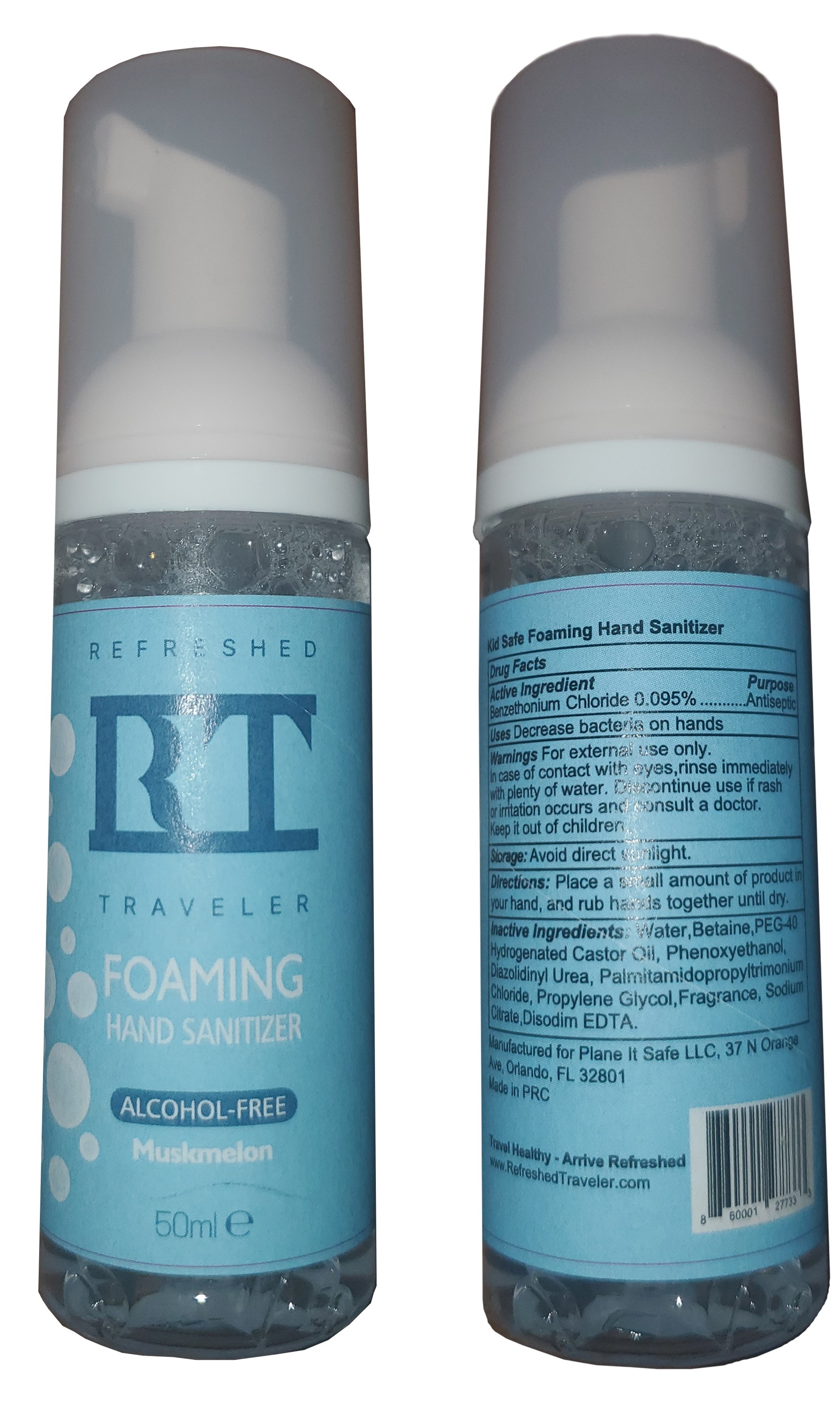 DRUG LABEL: Foaming Hand Sanitizer
NDC: 72920-2002 | Form: GEL
Manufacturer: Plane It Safe LLC
Category: otc | Type: HUMAN OTC DRUG LABEL
Date: 20211224

ACTIVE INGREDIENTS: BENZETHONIUM CHLORIDE 50 mg/50 mL
INACTIVE INGREDIENTS: WATER

Foaming Hand Sanitizer

Inactive Ingredients

Water,Betaine,PEG-40 Hydrogenated Castor Oil, Phenoxyethanol, Diazolidinyl Urea, Palmitamidopropyltrimonium Chloride, Propylene Glycol, Fragrance, Sodium Citrate, Disodim EDTA.

Active Ingredient:

Benzethonium Chloride (0.1%)

Directions:

Directions: Place a small amount of product in your hand and rub hands together until dry.

Uses:

Decrease bacteria on hands

Keep out of the reach of children

Warning:

For external use only. In case of contact with eyes,rinse immediately with plenty of water. Discontinue use if rash or irritation occurs and consult a doctor. Keep it out of children.

Purpose

Decrease Bacteria on hand